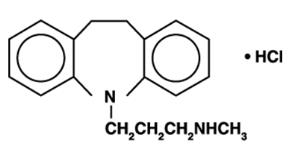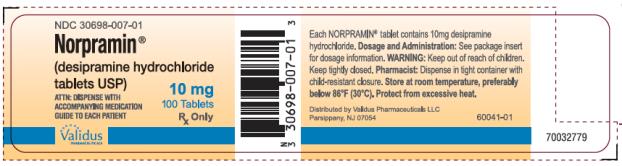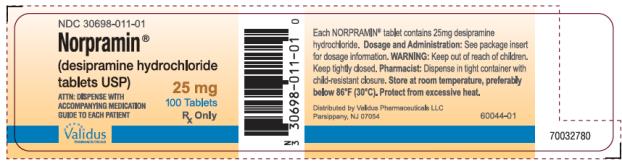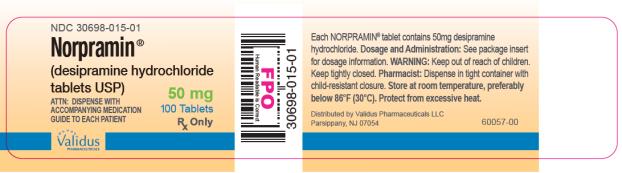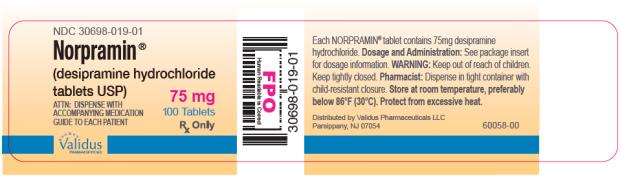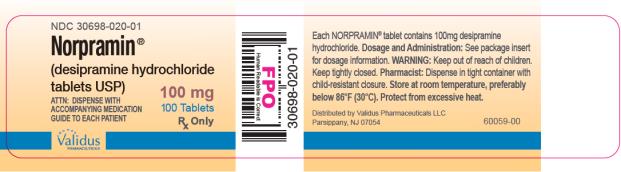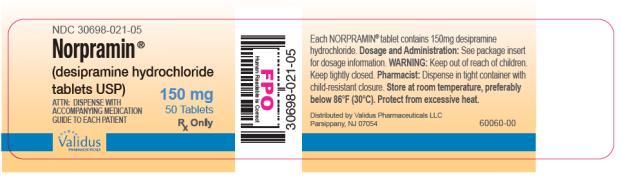 DRUG LABEL: Norpramin
NDC: 30698-007 | Form: TABLET, SUGAR COATED
Manufacturer: Validus Pharmaceuticals LLC
Category: prescription | Type: HUMAN PRESCRIPTION DRUG LABEL
Date: 20250703

ACTIVE INGREDIENTS: DESIPRAMINE HYDROCHLORIDE 10 mg/1 1
INACTIVE INGREDIENTS: ACACIA; CALCIUM CARBONATE; STARCH, CORN; D&C RED NO. 30; FD&C BLUE NO. 1; FERRIC OXIDE RED; LIGHT MINERAL OIL; MAGNESIUM STEARATE; MANNITOL; POLYETHYLENE GLYCOL 8000; SODIUM BENZOATE; SUCROSE; TALC; TITANIUM DIOXIDE

NORPRAMIN®
(desipramine hydrochloride tablets USP)

BOXED WARNING

Suicidality and Antidepressant Drugs

Antidepressants increased the risk compared to placebo of suicidal thinking and behavior (suicidality) in children, adolescents, and young adults in short-term studiesof major depressive disorder (MDD) and other psychiatric disorders. Anyone considering the use of NORPRAMIN or any other antidepressant in a child, adolescent, or young adult must balance this risk with the clinical need. Short-term studies did not show an increase in the risk of suicidality with antidepressants compared to placebo in adults beyond age 24; there was a reduction in risk with antidepressants compared to placebo in adults aged 65 and older. Depression and certain other psychiatric disorders are themselves associated with increases in the risk of suicide. Patients of all ages who are started on antidepressant therapy should be monitored appropriately and observed closely for clinical worsening, suicidality, or unusual changes in behavior. Families and caregivers should be advised of the need for close observation and communication with the prescriber. NORPRAMIN is not approved for use in pediatric patients. (see WARNINGS: Clinical Worsening and Suicide Risk, PRECAUTIONS: Information for Patients, and PRECAUTIONS: Pediatric Use).

DESCRIPTION

NORPRAMIN®(desipramine hydrochloride USP) is an antidepressant drug of the tricyclic type, and is chemically: 5 H-Dibenz[ bƒ]azepine-5-propanamine,10,11-dihydro- N-methyl-, monohydrochloride.

Each NORPRAMIN tablet contains 10 mg, 25 mg, 50 mg, 75 mg, 100 mg, or 150 mg of desipramine hydrochloride for oral administration.

Inactive Ingredients

The following inactive ingredients are contained in all dosage strengths: acacia, calcium carbonate, corn starch, D&C Red No. 30 and D&C Yellow No. 10 (except 10 mg and 150 mg), FD&C Blue No. 1 (except 25 mg, 75 mg, and 100 mg), hydrogenated soy oil, iron oxide, light mineral oil, magnesium stearate, mannitol, polyethylene glycol 8000, pregelatinized corn starch, sodium benzoate (except 150 mg), sucrose, talc, titanium dioxide, and other ingredients.

CLINICAL PHARMACOLOGY

Mechanism of Action

Available evidence suggests that many depressions have a biochemical basis in the form of a relative deficiency of neurotransmitters such as norepinephrine and serotonin. Norepinephrine deficiency may be associated with relatively low urinary 3-methoxy-4-hydroxyphenyl glycol (MHPG) levels, while serotonin deficiencies may be associated with low spinal fluid levels of 5-hydroxyindoleacetic acid.

While the precise mechanism of action of the tricyclic antidepressants is unknown, a leading theory suggests that they restore normal levels of neurotransmitters by blocking the re-uptake of these substances from the synapse in the central nervous system. Evidence indicates that the secondary amine tricyclic antidepressants, including NORPRAMIN, may have greater activity in blocking the re-uptake of norepinephrine. Tertiary amine tricyclic antidepressants, such as amitriptyline, may have greater effect on serotonin re-uptake.

NORPRAMIN is not a monoamine oxidase inhibitor (MAOI) and does not act primarily as a central nervous system stimulant. It has been found in some studies to have a more rapid onset of action than imipramine. Earliest therapeutic effects may occasionally be seen in 2 to 5 days, but full treatment benefit usually requires 2 to 3 weeks to obtain.

Metabolism

Tricyclic antidepressants, such as desipramine hydrochloride, are rapidly absorbed from the gastrointestinal tract. Tricyclic antidepressants or their metabolites are to some extent excreted through the gastric mucosa and reabsorbed from the gastrointestinal tract. Desipramine is metabolized in the liver, and approximately 70% is excreted in the urine.

The rate of metabolism of tricyclic antidepressants varies widely from individual to individual, chiefly on a genetically determined basis. Up to a 36-fold difference in plasma level may be noted among individuals taking the same oral dose of desipramine. The ratio of 2-hydroxydesipramine to desipramine may be increased in the elderly, most likely due to decreased renal elimination with aging.

Certain drugs, particularly the psychostimulants and the phenothiazines, increase plasma levels of concomitantly administered tricyclic antidepressants through competition for the same metabolic enzyme systems. Concurrent administration of cimetidine and tricyclic antidepressants can produce clinically significant increases in the plasma concentrations of the tricyclic antidepressants. Conversely, decreases in plasma levels of the tricyclic antidepressants have been reported upon discontinuation of cimetidine, which may result in the loss of the therapeutic efficacy of the tricyclic antidepressant. Other substances, particularly barbiturates and alcohol, induce liver enzyme activity and thereby reduce tricyclic antidepressant plasma levels. Similar effects have been reported with tobacco smoke.

Research on the relationship of plasma level to therapeutic response with the tricyclic antidepressants has produced conflicting results. While some studies report no correlation, many studies cite therapeutic levels for most tricyclics in the range of 50 to 300 nanograms per milliliter. The therapeutic range is different for each tricyclic antidepressant. For desipramine, an optimal range of therapeutic plasma levels has not been established.

INDICATIONS AND USAGE

NORPRAMIN is indicated for the treatment of depression.

CONTRAINDICATIONS

The use of MAOIs intended to treat psychiatric disorders with NORPRAMIN or within 14 days of stopping treatment with NORPRAMIN is contraindicated because of an increased risk of serotonin syndrome. The use of NORPRAMIN within 14 days of stopping an MAOI intended to treat psychiatric disorders is also contraindicated (see WARNINGSand DOSAGE AND ADMINISTRATION).

Starting NORPRAMIN in a patient who is being treated with MAOIs such as linezolid or intravenous methylene blue is also contraindicated because of an increased risk of serotonin syndrome (see WARNINGSand DOSAGE AND ADMINISTRATION).

NORPRAMIN is contraindicated in the acute recovery period following myocardial infarction. It should not be used in those who have shown prior hypersensitivity to the drug. Cross-sensitivity between this and other dibenzazepines is a possibility.

WARNINGS

Clinical Worsening and Suicide Risk

Patients with major depressive disorder (MDD), both adult and pediatric, may experience worsening of their depression and/or the emergence of suicidal ideation and behavior (suicidality) or unusual changes in behavior, whether or not they are taking antidepressant medications, and this risk may persist until significant remission occurs. Suicide is a known risk of depression and certain other psychiatric disorders, and these disorders themselves are the strongest predictors of suicide. There has been a long-standing concern, however, that antidepressants may have a role in inducing worsening of depression and the emergence of suicidality in certain patients during the early phases of treatment. Pooled analyses of short-term placebo-controlled trials of antidepressant drugs (selective serotonin re-uptake inhibitors [SSRIs] and others) showed that these drugs increase the risk of suicidal thinking and behavior (suicidality) in children, adolescents, and young adults (ages 18 to 24) with major depressive disorder (MDD) and other psychiatric disorders. Short-term studies did not show an increase in the risk of suicidality with antidepressants compared to placebo in adults beyond age 24; there was a reduction with antidepressants compared to placebo in adults aged 65 and older.

The pooled analyses of placebo-controlled trials in children and adolescents with MDD, obsessive compulsive disorder (OCD), or other psychiatric disorders included a total of 24 short-term trials of 9 antidepressant drugs in over 4400 patients. The pooled analyses of placebo-controlled trials in adults with MDD or other psychiatric disorders included a total of 295 short-term trials (median duration of 2 months) of 11 antidepressant drugs in over 77,000 patients. There was considerable variation in risk of suicidality among drugs, but a tendency toward an increase in the younger patients for almost all drugs studied. There were differences in absolute risk of suicidality across the different indications, with the highest incidence in MDD. The risk differences (drug vs. placebo), however, were relatively stable within age strata and across indications. These risk differences (drug-placebo difference in the number of cases of suicidality per 1000 patients treated) are provided in Table 1.

Table 1
Age Range | Drug-Placebo Difference in Number of Cases of Suicidality per 1000 Patients Treated
 | Increases Compared to Placebo
<18 | 14 additional cases
18-24 | 5 additional cases
 | Decreases Compared to Placebo
25-64 | 1 fewer case
≥65 | 6 fewer cases

No suicides occurred in any of the pediatric trials. There were suicides in the adult trials, but the number was not sufficient to reach any conclusion about drug effect on suicide.

It is unknown whether the suicidality risk extends to longer-term use, i.e., beyond several months. However, there is substantial evidence from placebo-controlled maintenance trials in adults with depression that the use of antidepressants can delay the recurrence of depression.

All patients being treated with antidepressants for any indication should bemonitored appropriately andobserved closely for clinical worsening, suicidality, and unusual changes in behavior, especially during the initial few months of a course of drug therapy, or at times of dose changes, either increases or decreases.

The following symptoms, anxiety, agitation, panic attacks, insomnia, irritability, hostility, aggressiveness, impulsivity, akathisia (psychomotor restlessness), hypomania, and mania, have been reported in adult and pediatric patients being treated with antidepressants for major depressive disorder as well as for other indications, both psychiatric and nonpsychiatric. Although a causal link between the emergence of such symptoms and either the worsening of depression and/or the emergence of suicidal impulses has not been established, there is concern that such symptoms may represent precursors to emerging suicidality.

Consideration should be given to changing the therapeutic regimen, including possibly discontinuing the medication, in patients whose depression is persistently worse, or who are experiencing emergent suicidality or symptoms that might be precursors to worsening depression or suicidality, especially if these symptoms are severe, abrupt in onset, or were not part of the patient's presenting symptoms.

Families and caregivers of patients being treated with antidepressants for major depressive disorder or other indications, both psychiatric and nonpsychiatric, should be alerted about the need to monitor patients for the emergence of agitation, irritability, unusual changes in behavior, and the other symptoms described above, as well as the emergence of suicidality, and to report such symptoms immediately to health care providers. Such monitoring should include daily observation by families and caregivers.Prescriptions for NORPRAMIN should be written for the smallest quantity of tablets consistent with good patient management, in order to reduce the risk of overdose.

Screening Patients for Bipolar Disorder:A major depressive episode may be the initial presentation of bipolar disorder. It is generally believed (though not established in controlled trials) that treating such an episode with an antidepressant alone may increase the likelihood of precipitation of a mixed/manic episode in patients at risk for bipolar disorder. Whether any of the symptoms described above represent such a conversion is unknown. However, prior to initiating treatment with an antidepressant, patients with depressive symptoms should be adequately screened to determine if they are at risk for bipolar disorder; such screening should include a detailed psychiatric history, including a family history of suicide, bipolar disorder, and depression. It should be noted that NORPRAMIN is not approved for use in treating bipolar depression.

Serotonin Syndrome:The development of a potentially life-threatening serotonin syndrome has been reported with serotonin norepinephrine re-uptake inhibitors (SNRIs) and SSRIs, including NORPRAMIN, alone but particularly with concomitant use of other serotonergic drugs (including triptans, tricyclic antidepressants, fentanyl, lithium, tramadol, tryptophan, buspirone, and St. John’s Wort) and with drugs that impair metabolism of serotonin (in particular, MAOIs both those intended to treat psychiatric disorders and also others, such as linezolid and intravenous methylene blue).

Serotonin syndrome symptoms may include mental status changes (e.g., agitation, hallucinations, delirium, and coma), autonomic instability (e.g., tachycardia, labile blood pressure, dizziness, diaphoresis, flushing, hyperthermia), neuromuscular changes (e.g., tremor, rigidity, myoclonus, hyperreflexia, incoordination), seizures, and/or gastrointestinal symptoms (e.g., nausea, vomiting, diarrhea). Patients should be monitored for the emergence of serotonin syndrome.

The concomitant use of NORPRAMIN with MAOIs intended to treat psychiatric disorders is contraindicated. NORPRAMIN should also not be started in a patient who is being treated with MAOIs such as linezolid or intravenous methylene blue. All reports with methylene blue that provided information on the route of administration involved intravenous administration in the dose range of 1 mg/kg to 8 mg/kg. No reports involved the administration of methylene blue by other routes (such as oral tablets or local tissue injection) or at lower doses. There may be circumstances when it is necessary to initiate treatment with an MAOI such as linezolid or intravenous methylene blue in a patient taking NORPRAMIN. NORPRAMIN should be discontinued before initiating treatment with the MAOI (see CONTRAINDICATIONSand DOSAGE AND ADMINISTRATION).

If concomitant use of NORPRAMIN with other serotonergic drugs including triptans, tricyclic antidepressants, fentanyl, lithium, tramadol, buspirone, tryptophan, and St. John’s Wort is clinically warranted, patients should be made aware of a potential increased risk for serotonin syndrome particularly during treatment initiation and dose increases.

Treatment with NORPRAMIN and any concomitant serotonergic agents should be discontinued immediately if the above events occur and supportive symptomatic treatment should be initiated.

Hyponatremia- Hyponatremia has occurred as a result of treatment with NORPRAMIN. In many cases, hyponatremia appears to be the result of the syndrome of inappropriate antidiuretic hormone secretion (SIADH). Signs and symptoms of hyponatremia include headache, difficulty concentrating, memory impairment, confusion, weakness, and unsteadiness, which may lead to falls. Signs and symptoms associated with more severe and/or acute cases have included syncope, seizure, coma, respiratory arrest, and death.

In patients with symptomatic hyponatremia, discontinue NORPRAMIN and institute appropriate medical intervention. Elderly patients, patients taking diuretics, and those who are volume-depleted may be at greater risk of developing hyponatremia with NORPRAMIN.

Angle-Closure Glaucoma:The pupillary dilation that occurs following use of many antidepressant drugs including Norpramin may trigger an angle closure attack in a patient with anatomically narrow angles who does not have a patent iridectomy.

General

Extreme caution should be used when this drug is given in the following situations:

a. In patients with cardiovascular disease, because of the possibility of conduction defects, arrhythmias, tachycardias, strokes, and acute myocardial infarction.
b. In patients who have a family history of sudden death, cardiac dysrhythmias, or cardiac conduction disturbances.
c. In patients with a history of urinary retention or glaucoma, because of the anticholinergic properties of the drug.
d. In patients with thyroid disease or those taking thyroid medication, because of the possibility of cardiovascular toxicity, including arrhythmias.
e. In patients with a history of seizure disorder, because this drug has been shown to lower the seizure threshold. Seizures precede cardiac dysrhythmias and death in some patients.

This drug is capable of blocking the antihypertensive effect of guanethidine and similarly acting compounds.

The patient should be cautioned that this drug may impair the mental and/or physical abilities required for the performance of potentially hazardous tasks such as driving a car or operating machinery.

In patients who may use alcohol excessively, it should be borne in mind that the potentiation may increase the danger inherent in any suicide attempt or overdosage.

Pregnancy

There is a pregnancy exposure registry that monitors pregnancy outcomes in women exposed to antidepressants, including NORPRAMIN, during pregnancy. Healthcare providers are encouraged to register patients by calling the National Pregnancy Registry for Antidepressants at 1-844-405-6185 or visiting online at http://womensmentalhealth.org/clinical-and-research-programs/pregnancyregistry/antidepressants

Safe use of NORPRAMIN during pregnancy and lactation has not been established; therefore, if it is to be given to pregnant patients, nursing mothers, or women of childbearing potential, the possible benefits must be weighed against the possible hazards to mother and child. Animal reproductive studies have been inconclusive.

Geriatric Use

Clinical studies of NORPRAMIN did not include sufficient numbers of subjects aged 65 and over to determine whether they respond differently from younger subjects. Other reported clinical experience has not identified differences in responses between the elderly and younger patients. Lower doses are recommended for elderly patients (see DOSAGE AND ADMINISTRATION).

The ratio of 2-hydroxydesipramine to desipramine may be increased in the elderly, most likely due to decreased renal elimination with aging.

This drug is known to be substantially excreted by the kidney, and the risk of toxic reactions to this drug may be greater in patients with impaired renal function. Because elderly patients are more likely to have decreased renal function, care should be taken in dose selection, and it may be useful to monitor renal function.

NORPRAMIN use in the elderly has been associated with a proneness to falling as well as confusional states (see ADVERSE REACTIONS).

PRECAUTIONS

Information for Patients

Prescribers or other health professionals should inform patients, their families, and their caregivers about the benefits and risks associated with treatment with NORPRAMIN and should counsel them in its appropriate use. A patient Medication Guide about “Antidepressant Medicines, Depression and other Serious Mental Illnesses, and Suicidal Thoughts or Actions” is available for NORPRAMIN. The prescriber or health professional should instruct patients, their families, and their caregivers to read the Medication Guide and should assist them in understanding its contents. Patients should be given the opportunity to discuss the contents of the Medication Guide and to obtain answers to any questions they may have. The complete text of the Medication Guide is reprinted at the end of this document.

Patients should be advised of the following issues and asked to alert their prescriber if these occur while taking NORPRAMIN.

Clinical Worsening and Suicide Risk: Patients, their families, and their caregivers should be encouraged to be alert to the emergence of anxiety, agitation, panic attacks, insomnia, irritability, hostility, aggressiveness, impulsivity, akathisia (psychomotor restlessness), hypomania, mania, other unusual changes in behavior, worsening of depression, and suicidal ideation, especially early during antidepressant treatment and when the dose is adjusted up or down. Families and caregivers of patients should be advised to observe for the emergence of such symptoms on a day-to-day basis, since changes may be abrupt. Such symptoms should be reported to the patient's prescriber or health professional, especially if they are severe, abrupt in onset, or were not part of the patient's presenting symptoms. Symptoms such as these may be associated with an increased risk for suicidal thinking and behavior and indicate a need for very close monitoring and possibly changes in the medication.

Patients should be advised that taking Norpramin can cause mild pupillary dilation, which in susceptible individuals, can lead to an episode of angle closure glaucoma. Pre-existing glaucoma is almost always open-angle glaucoma because angle closure glaucoma, when diagnosed, can be treated definitively with iridectomy. Open-angle glaucoma is not a risk factor for angle closure glaucoma. Patients may wish to be examined to determine whether they are susceptible to angle closure, and have a prophylactic procedure (e.g., iridectomy), if they are susceptible.

Pediatric Use

Safety and effectiveness in the pediatric population have not been established (see BOX WARNINGand WARNINGS-Clinical Worsening and Suicide Risk). Therefore, NORPRAMIN (desipramine hydrochloride) is not recommended for use in children.

Anyone considering the use of NORPRAMIN in a child or adolescent must balance the potential risks with the clinical need (see also ADVERSE REACTIONS-Cardiovascular).

General

It is important that this drug be dispensed in the least possible quantities to depressed outpatients, since suicide has been accomplished with this class of drug (see WARNINGS-Clinical Worsening and Suicide Risk). Ordinary prudence requires that children not have access to this drug or to potent drugs of any kind; if possible, this drug should be dispensed in containers with child-resistant safety closures. Storage of this drug in the home must be supervised responsibly.

If serious adverse effects occur, dosage should be reduced or treatment should be altered.

NORPRAMIN therapy in patients with manic-depressive illness may induce a hypomanic state after the depressive phase terminates.

The drug may cause exacerbation of psychosis in schizophrenic patients.

Both elevation and lowering of blood sugar levels have been reported.

Leukocyte and differential counts should be performed in any patient who develops fever and sore throat during therapy; the drug should be discontinued if there is evidence of pathologic neutrophil depression.

Clinical experience in the concurrent administration of ECT and antidepressant drugs is limited. Thus, if such treatment is essential, the possibility of increased risk relative to benefits should be considered.

This drug should be discontinued as soon as possible prior to elective surgery because of possible cardiovascular effects. Hypertensive episodes have been observed during surgery in patients taking desipramine hydrochloride.

Drug Interactions

Drugs Metabolized by P450 2D6.

The biochemical activity of the drug metabolizing isozyme cytochrome P450 2D6 (debrisoquin hydroxylase) is reduced in a subset of the Caucasian population (about 7% to 10% of Caucasians are so called “poor metabolizers”); reliable estimates of the prevalence of reduced P450 2D6 isozyme activity among Asian, African and other populations are not yet available. Poor metabolizers have higher than expected plasma concentrations of tricyclic antidepressants (TCAs) when given usual doses. Depending on the fraction of drug metabolized by P450 2D6, the increase in plasma concentration may be small, or quite large (8 fold increase in plasma AUC of the TCA).

In addition, certain drugs inhibit the activity of this isozyme and make normal metabolizers resemble poor metabolizers. An individual who is stable on a given dose of TCA may become abruptly toxic when given one of these inhibiting drugs as concomitant therapy. The drugs that inhibit cytochrome P450 2D6 include some that are not metabolized by the enzyme (quinidine; cimetidine) and many that are substrates for P450 2D6 (many other antidepressants, phenothiazines, and the Type IC antiarrhythmics propafenone and flecainide). While all the SSRIs, e.g., fluoxetine, sertraline, paroxetine, inhibit P450 2D6, they may vary in the extent of inhibition. The extent to which SSRI TCA interactions may pose clinical problems will depend on the degree of inhibition and the pharmacokinetics of the SSRI involved. Nevertheless, caution is indicated in the co-administration of TCAs with any of the SSRIs and also in switching from one class to the other. Of particular importance, sufficient time must elapse before initiating TCA treatment in a patient being withdrawn from fluoxetine, given the long half-life of the parent and active metabolite (at least 5 weeks may be necessary).

Concomitant use of tricyclic antidepressants with drugs that can inhibit cytochrome P450 2D6 may require lower doses than usually prescribed for either the tricyclic antidepressant or the other drug. Furthermore, whenever one of these other drugs is withdrawn from co-therapy, an increased dose of tricyclic antidepressant may be required. It is desirable to monitor TCA plasma levels whenever a TCA is going to be co-administered with another drug known to be an inhibitor of P450 2D6.

Close supervision and careful adjustment of dosage are required when this drug is given concomitantly with anticholinergic or sympathomimetic drugs.

Patients should be warned that while taking this drug their response to alcoholic beverages may be exaggerated.

If NORPRAMIN is to be combined with other psychotropic agents such as tranquilizers or sedative/hypnotics, careful consideration should be given to the pharmacology of the agents employed since the sedative effects of NORPRAMIN and benzodiazepines (e.g., chlordiazepoxide or diazepam) are additive. Both the sedative and anticholinergic effects of the major tranquilizers are also additive to those of NORPRAMIN.

Concomitant use of Monoamine Oxidase Inhibitors (MAOIs) and serotonergic drugs may potentially cause life threatening adverse events (see CONTRAINDICATIONS, WARNINGS, and DOSAGE AND ADMINISTRATION).

ADVERSE REACTIONS

Included in the following listing are a few adverse reactions that have not been reported with this specific drug. However, the pharmacologic similarities among the tricyclic antidepressant drugs require that each of the reactions be considered when NORPRAMIN is given.

Cardiovascular: Hypotension, hypertension, palpitations, heart block, myocardial infarction, stroke, arrhythmias, premature ventricular contractions, tachycardia, ventricular tachycardia, ventricular fibrillation, sudden death

There has been a report of an "acute collapse" and "sudden death" in an 8-year-old (18 kg) male, treated for 2 years for hyperactivity.

There have been additional reports of sudden death in children (see PRECAUTIONS-Pediatric Use).

Psychiatric: Confusional states (especially in the elderly) with hallucinations, disorientation, delusions; anxiety, restlessness, agitation; insomnia and nightmares; hypomania; exacerbation of psychosis

Neurologic: Numbness, tingling, paresthesias of extremities; incoordination, ataxia, tremors; peripheral neuropathy; extrapyramidal symptoms; seizures; alterations in EEG patterns; tinnitus

Symptoms attributed to Neuroleptic Malignant Syndrome have been reported during desipramine use with and without concomitant neuroleptic therapy.

Anticholinergic: Dry mouth, and rarely associated sublingual adenitis; blurred vision, disturbance of accommodation, mydriasis, increased intraocular pressure; constipation, paralytic ileus; urinary retention, delayed micturition, dilation of urinary tract

Allergic: Skin rash, petechiae, urticaria, itching, photosensitization (avoid excessive exposure to sunlight), edema (of face and tongue or general), drug fever, cross-sensitivity with other tricyclic drugs

Hematologic: Bone marrow depressions including agranulocytosis, eosinophilia, purpura, thrombocytopenia

Gastrointestinal: Anorexia, nausea and vomiting, epigastric distress, peculiar taste, abdominal cramps, diarrhea, stomatitis, black tongue, hepatitis, jaundice (simulating obstructive), altered liver function, elevated liver function tests, increased pancreatic enzymes

Endocrine: Gynecomastia in the male, breast enlargement and galactorrhea in the female; increased or decreased libido, impotence, painful ejaculation, testicular swelling; elevation or depression of blood sugar levels; syndrome of inappropriate antidiuretic hormone secretion (SIADH)

Other: Weight gain or loss; perspiration, flushing; urinary frequency, nocturia; parotid swelling; drowsiness, dizziness, proneness to falling, weakness and fatigue, headache; fever; alopecia; elevated alkaline phosphatase, hyponatremia.

Withdrawal Symptoms: Though not indicative of addiction, abrupt cessation of treatment after prolonged therapy may produce nausea, headache, and malaise.

To report SUSPECTED ADVERSE REACTIONS, contact Validus Pharmaceuticals LLC at 1-866-982-5438 (1-866-9VALIDUS) or FDA at 1-800-FDA-1088 or www.fda.gov/medwatch.

OVERDOSAGE

Deaths may occur from overdosage with this class of drugs. Overdose of desipramine has resulted in a higher death rate compared to overdoses of other tricyclic antidepressants. Multiple drug ingestion (including alcohol) is common in deliberate tricyclic antidepressant overdose. As the management is complex and changing, it is recommended that the physician contact a poison control center for current information on treatment. Signs and symptoms of toxicity develop rapidly after tricyclic antidepressant overdose; therefore, hospital monitoring is required as soon as possible. There is no specific antidote for desipramine overdosage.

Oral LD50

The oral LD50of desipramine is 290 mg/kg in male mice and 320 mg/kg in female rats.

Manifestations of Overdosage

Critical manifestations of overdose include: cardiac dysrhythmias, severe hypotension, convulsions, and CNS depression, including coma. Changes in the electrocardiogram, particularly in QRS axis or width, are clinically significant indicators of tricyclic antidepressant toxicity. Early changes in the QRS complex include a widening of the terminal 40 msec with a rightward axis in the frontal plane, recognized by the presence of a terminal S wave in Lead 1 and AVL and an R wave in AVR.

Other signs of overdose may include: confusion, disturbed concentration, transient visual hallucinations, dilated pupils, agitation, hyperactive reflexes, stupor, drowsiness, muscle rigidity, vomiting, hypothermia, hyperpyrexia, or any of the symptoms listed under ADVERSE REACTIONS.

Management

Aggressive supportive care and serum alkalinization are the mainstays of therapy.

General. Obtain an ECG and immediately initiate cardiac monitoring. Protect the patient’s airway, establish an intravenous line, and initiate gastric decontamination. A minimum of 6 hours of observation with cardiac monitoring and observation for signs of CNS or respiratory depression, hypotension, cardiac dysrhythmias and/or conduction blocks, and seizures is necessary. If signs of toxicity occur at any time during this period, extended monitoring is required. Follow ECG, renal function, CPK, and arterial blood gases as clinically indicated. There are case reports of patients succumbing to fatal dysrhythmias late after overdose; these patients had clinical evidence of significant poisoning prior to death, and most received inadequate gastrointestinal decontamination. Monitoring of plasma drug levels should not guide management of the patient.

Gastrointestinal Decontamination.Emesis is contraindicated. Activated charcoal should be administered to patients who present early after an overdose.

Cardiovascular.A maximal limb-lead QRS duration widening to greater than 100 msec is a significant indicator of toxicity, specifically for the risk of seizures and, eventually, cardiac dysrhythmias. Serum alkalinization with intravenous sodium bicarbonate and hyperventilation (as needed) should be instituted in patients manifesting significant toxicity such as QRS widening. Dysrhythmias despite adequate alkalemia may respond to overdrive pacing, beta-agonist infusions, and magnesium therapy. Type 1A and 1C antiarrhythmics are generally contraindicated (e.g., quinidine, disopyramide, and procainamide).

CNS.In patients with CNS depression, early intubation is advised because of the potential for abrupt deterioration. Seizures should be controlled with benzodiazepines. If these are ineffective or seizures recur, other anticonvulsants (e.g.., phenobarbital, propofol) may be used.

Psychiatric Follow-up. Since overdosage is often deliberate, patients may attempt suicide by other means during the recovery phase. Psychiatric referral may be appropriate.

Pediatric Management. The principles of management of child and adult overdosages are similar. It is strongly recommended that the physician contact the local poison control center for specific pediatric treatment.

DOSAGE AND ADMINISTRATION

Not recommended for use in children (see WARNINGS).

Lower dosages are recommended for elderly patients and adolescents. Lower dosages are also recommended for outpatients compared to hospitalized patients, who are closely supervised. Dosage should be initiated at a low level and increased according to clinical response and any evidence of intolerance. Following remission, maintenance medication may be required for a period of time and should be at the lowest dose that will maintain remission.

Usual Adult Dose

The usual adult dose is 100 mg to 200 mg per day. In more severely ill patients, dosage may be further increased gradually to 300 mg/day if necessary. Dosages above 300 mg/day are not recommended.

Dosage should be initiated at a lower level and increased according to tolerance and clinical response.

Treatment of patients requiring as much as 300 mg should generally be initiated in hospitals, where regular visits by the physician, skilled nursing care, and frequent electrocardiograms (ECGs) are available.

The best available evidence of impending toxicity from very high doses of NORPRAMIN is prolongation of the QRS or QT intervals on the ECG. Prolongation of the PR interval is also significant, but less closely correlated with plasma levels. Clinical symptoms of intolerance, especially drowsiness, dizziness, and postural hypotension, should also alert the physician to the need for reduction in dosage.

Initial therapy may be administered in divided doses or a single daily dose.

Maintenance therapy may be given on a once-daily schedule for patient convenience and compliance.

Adolescent and Geriatric Dose

The usual adolescent and geriatric dose is 25 mg to 100 mg daily.

Dosage should be initiated at a lower level and increased according to tolerance and clinical response to a usual maximum of 100 mg daily. In more severely ill patients, dosage may be further increased to 150 mg/day. Doses above 150 mg/day are not recommended in these age groups.

Initial therapy may be administered in divided doses or a single daily dose.

Maintenance therapy may be given on a once-daily schedule for patient convenience and compliance.

Switching a Patient To or From a Monoamine Oxidase Inhibitor (MAOI) Intended to Treat Psychiatric Disorders: At least 14 days should elapse between discontinuation of an MAOI intended to treat psychiatric disorders and initiation of therapy with NORPRAMIN. Conversely, at least 14 days should be allowed after stopping NORPRAMIN before starting an MAOI intended to treat psychiatric disorders (see CONTRAINDICATIONS).

Use of NORPRAMIN With Other MAOI’s Such as Linezolid or Methylene Blue:

Do not start NORPRAMIN in a patient who is being treated with linezolid or intravenous methylene blue because there is increased risk of serotonin syndrome. In a patient who requires more urgent treatment of a psychiatric condition, other interventions, including hospitalization, should be considered (see CONTRAINDICATIONS).

In some cases, a patient already receiving NORPRAMIN therapy may require urgent treatment with linezolid or intravenous methylene blue. If acceptable alternatives to linezolid or intravenous methylene blue treatment are not available and the potential benefits of linezolid or intravenous methylene blue treatment are judged to outweigh the risks of serotonin syndrome in a particular patient, NORPRAMIN should be stopped promptly, and linezolid or intravenous methylene blue can be administered. The patient should be monitored for symptoms of serotonin syndrome for 2 weeks or until 24 hours after the last dose of linezolid or intravenous methylene blue, whichever comes first. Therapy with NORPRAMIN may be resumed 24 hours after the last dose of linezolid or intravenous methylene blue (see WARNINGS).

The risk of administering methylene blue by non-intravenous routes (such as oral tablets or by local injection) or in intravenous doses much lower than 1 mg/kg with NORPRAMIN is unclear. The clinician should, nevertheless, be aware of the possibility of emergent symptoms of serotonin syndrome with such use (see WARNINGS).

HOW SUPPLIED

10 mg blue coated tablets imprinted 68-7
NDC 30698-007-01: bottles of 100

25 mg yellow coated tablets imprinted NORPRAMIN 25
NDC 30698-011-01: bottles of 100

50 mg green coated tablets imprinted NORPRAMIN 50
NDC 30698-015-01: bottles of 100

75 mg orange coated tablets imprinted NORPRAMIN 75
NDC 30698-019-01: bottles of 100

100 mg peach coated tablets imprinted NORPRAMIN 100
NDC 30698-020-01: bottles of 100

150 mg white coated tablets imprinted NORPRAMIN 150
NDC 30698-021-05-: bottles of 50

Store at 77oF (25oC); excursions permitted to 59oto86oF (15oto 30oC) [See USP Controlled Room Temperature].

Dispense in a tight container. Protect from excessive heat.

Rx Only

Manufactured for and Distributed by:

Validus Pharmaceuticals LLC

119 Cherry Hill Road, Suite 310

Parsippany, NJ 07054
info@validuspharma.com
www.validuspharma.com
1-866-982-5438 (1-866-9VALIDUS)

Product of Finland

© 2018 Validus Pharmaceuticals LLC

60040-02 November 2018

Medication Guide

Norpramin®(desipramine hydrochloride tablets USP)

Antidepressant Medicines, Depression and other Serious Mental Illnesses, and Suicidal Thoughts or Actions

Read the Medication Guide that comes with your or your family member’s, antidepressant medicine. This Medication Guide is only about the risk of suicidal thoughts and actions with antidepressant medicines. Talk toyouror your family member’s, healthcare provider about:

- all risks and benefits of treatment with antidepressant medicines
- all treatment choices for depression or other serious mental illness

What is the most important information I should knowabout antidepressant medicines, depression and other serious mental illnesses, and suicidal thoughts or actions?

1. Antidepressant medicines may increase suicidal thoughts or actions in some children, teenagers, and young ad within the first few months of treatment.

2. Depression and other serious mental illnesses are the most important causes of suicidal thoughts and actions. Some people may have a particularly high risk of having suicidal thoughts or actions.These include people who have (or have a family history of) bipolar illness (also called manic-depressive illness) or suicidal thoughts or actions.

3.How can I watch for and try to prevent suicidal thoughts and actions in myself or a family member?

- Pay close attention to any changes, especially sudden changes, in mood, behaviors, thoughts, or feelings. This is very important when an antidepressant medicine is started or when the dose is changed.
- Call the healthcare provider right away to report new or sudden changes in mood, behavior, thoughts, or feelings.
- Keep all follow-up visits with the healthcare provider as scheduled. Call the healthcare provider between visits as needed, especially if you have concerns about symptoms.

Who should not take NORPRAMIN?

- You should not take NORPRAMIN if you take a monoamine oxidase inhibitor (MAOI). Ask your healthcare provider or pharmacist if you are not sure if you take an MAOI, including the antibiotic linezolid.
- Do not take an MAOI within 2 weeks of stopping NORPRAMIN unless directed to do so by your physician.
- Do not start NORPRAMIN if you stopped taking an MAOI in the last 2 weeks unless directed to do so by your physician.

Call a healthcare provider right away if you or your family member has any of the following symptoms, especially if they are new, worse, or worry you:

- thoughts about suicide or dying
- attempts to commit suicide
- new or worse depression
- new or worse anxiety
- feeling very agitated or restless
- panic attacks
- trouble sleeping (insomnia)
- new or worse irritability
- acting aggressive, being angry, or violent
- acting on dangerous impulses
- an extreme increase in activity and talking (mania)
- other unusual changes in behavior or mood

Low salt (sodium) levels in the blood. Elderly people may be at greater risk for this. Symptoms may include:

- headache
- weakness or feeling unsteady
- confusion, problems concentrating or thinking or memory problems

Visual Problems

- eye pain
- changes in vision
- swelling or redness in or around the eye
  Only some people are at risk for these problems. You may want to undergo an eye examination to see if you are at risk and receive preventative treatment if you are.

What else do I need to know about antidepressant medicines?

- Never stop an antidepressant medicine without first talking to a healthcare provider.Stopping an antidepressant medicine suddenly can cause other symptoms.
- Antidepressants are medicines used to treat depression and other illnesses.It is important to discuss all the risks of treating depression and also the risks of not treating it. Patients and their families or other caregivers should discuss all treatment choices with the healthcare provider, not just the use of antidepressants.
- Antidepressant medicines have other side effects.Talk to the healthcare provider about the side effects of the medicine prescribed for you or your family member.
- Antidepressant medicines can interact with other medicines.Know all of the medicines that you or your family member takes. Keep a list of all medicines to show the healthcare provider. Do not start new medicines without first checking with your healthcare provider.
- Not all antidepressant medicines prescribed for children are FDA approved for use in children.Talk to your child’s healthcare provider for more information.
- Tell your healthcare provider if you are pregnant or plan to become pregnant during treatment with Norpramin.
  ○ If you become pregnant during treatment with Norpramin, talk to your healthcare provider about registering with the National Pregnancy Registry for Antidepressants. You can register by calling 1-844-405-6185 or visit http://womensmentalhealth.org/clinical-and-research-programs/pregnancyregistry/antidepressants
- Tell your healthcare provider if you have low sodium levels in your blood during treatment with Norpramin.

Call your doctor for medical advice about side effects. You may report side effects to FDA at 1-800-FDA-1088.

You may also report side effects to Validus Pharmaceuticals LLC U.S. at 1-866-982-5438 (1-866-9VALIDUS).

This Medication Guide has been approved by the U.S. Food and Drug Administration.

Manufactured for and Distributed by:

Validus Pharmaceuticals LLC

119 Cherry Hill Road, Suite 310

Parsippany, NJ 07054
info@validuspharma.com
www.validuspharma.com
1-866-982-5438 (1-866-9VALIDUS)

Product of Finland

© 2018 Validus Pharmaceuticals LLC

60040-03 June 2025

PRINCIPAL DISPLAY PANEL

NDC 30698-007-01

Norpramin®
(desipramine hydrochloride
tablets USP)

10 mg
100 Tablets

PRINCIPAL DISPLAY PANEL

NDC 30698-011-01

Norpramin®
(desipramine hydrochloride
tablets USP)

25 mg
100 Tablets

PRINCIPAL DISPLAY PANEL

NDC 30698-015-01

Norpramin®
(desipramine hydrochloride
tablets USP)

50 mg
100 Tablets

PRINCIPAL DISPLAY PANEL

NDC 30698-019-01

Norpramin®
(desipramine hydrochloride
tablets USP)

75 mg
100 Tablets

PRINCIPAL DISPLAY PANEL

NDC 30698-020-01

Norpramin®
(desipramine hydrochloride
tablets USP)

100 mg
100 Tablets

PRINCIPAL DISPLAY PANEL

NDC 30698-021-01

Norpramin®
(desipramine hydrochloride
tablets USP)

150 mg
100 Tablets